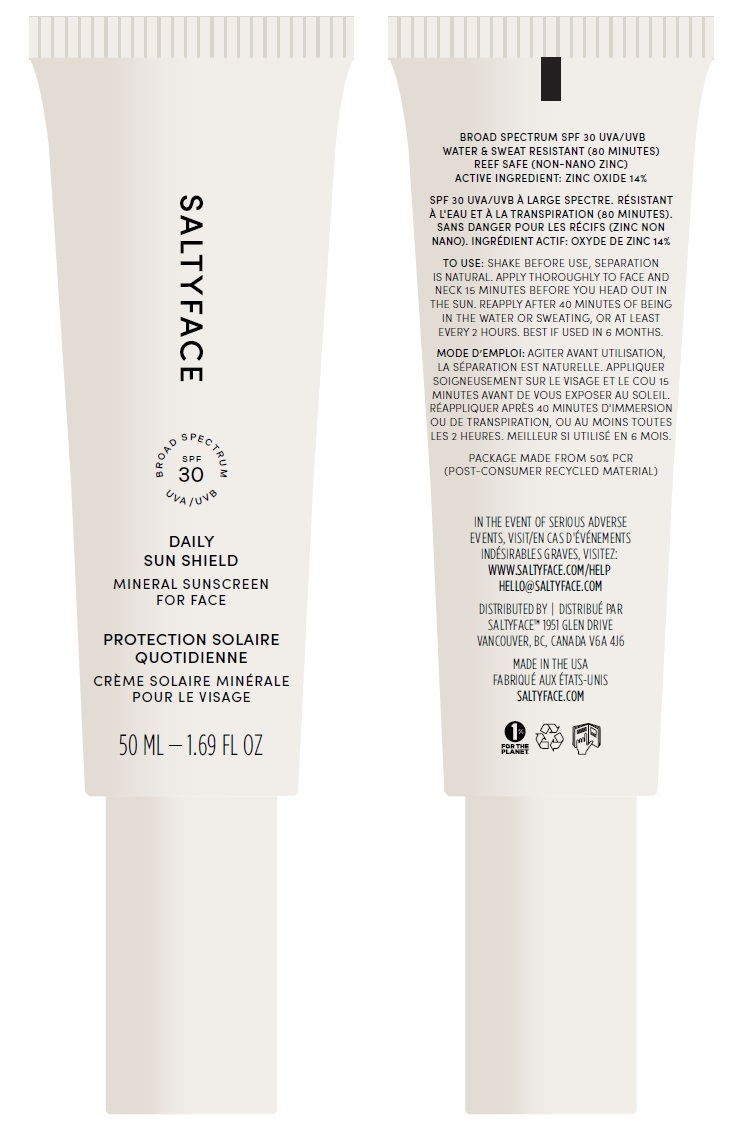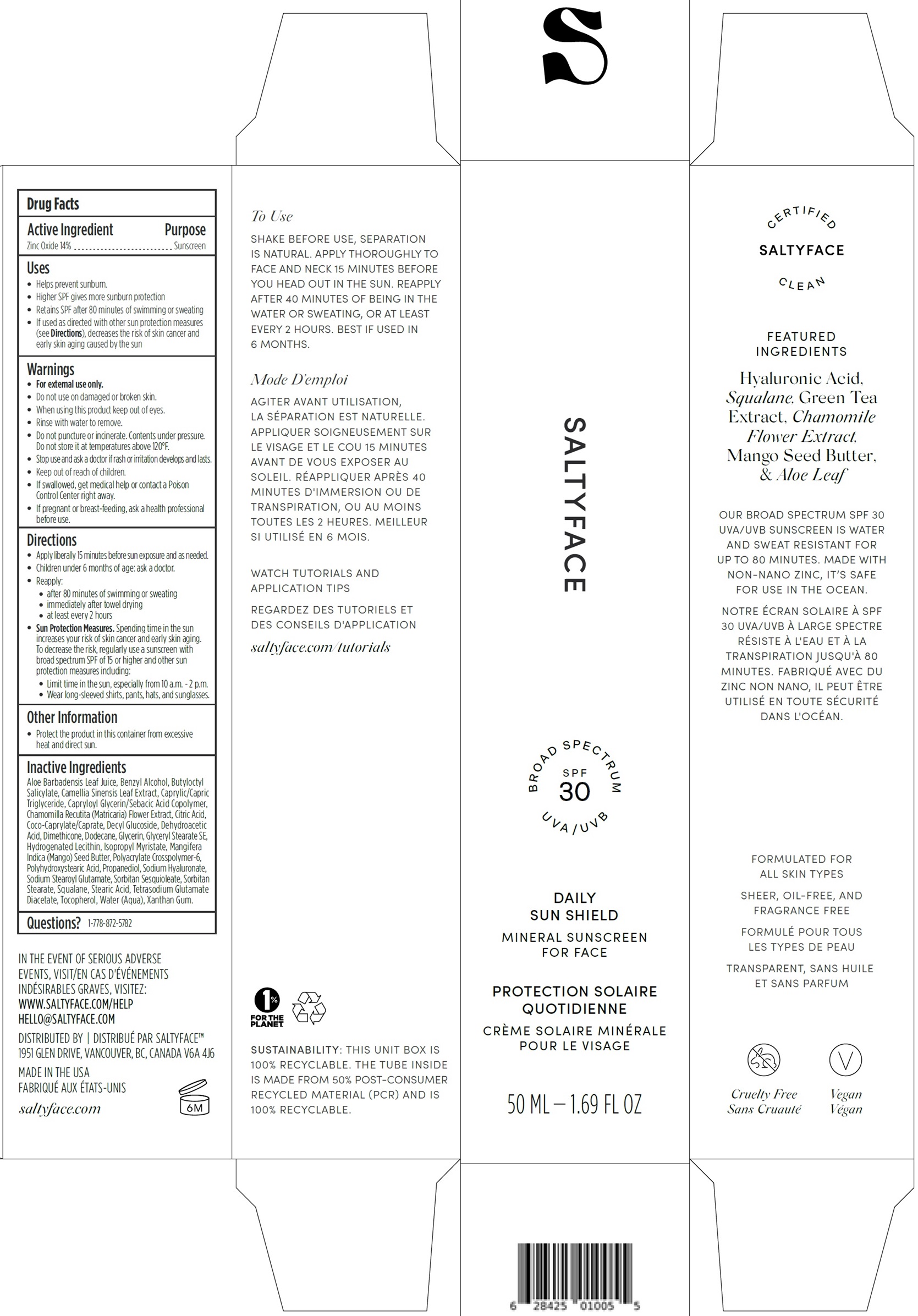 DRUG LABEL: SaltyFace Daily Sun Shield Mineral Sunscreen For Face SPF 30
NDC: 85046-574 | Form: CREAM
Manufacturer: Saltyface Natural Inc
Category: otc | Type: HUMAN OTC DRUG LABEL
Date: 20241218

ACTIVE INGREDIENTS: ZINC OXIDE 140 mg/1 mL
INACTIVE INGREDIENTS: ALOE VERA LEAF; BENZYL ALCOHOL; BUTYLOCTYL SALICYLATE; GREEN TEA LEAF; MEDIUM-CHAIN TRIGLYCERIDES; CHAMOMILE; CITRIC ACID MONOHYDRATE; COCOYL CAPRYLOCAPRATE; DECYL GLUCOSIDE; DEHYDROACETIC ACID; DIMETHICONE; DODECANE; GLYCERIN; GLYCERYL STEARATE SE; ISOPROPYL MYRISTATE; MANGIFERA INDICA SEED BUTTER; AMMONIUM ACRYLOYLDIMETHYLTAURATE, DIMETHYLACRYLAMIDE, LAURYL METHACRYLATE AND LAURETH-4 METHACRYLATE COPOLYMER, TRIMETHYLOLPROPANE TRIACRYLATE CROSSLINKED (45000 MPA.S); PROPANEDIOL; HYALURONATE SODIUM; SODIUM STEAROYL GLUTAMATE; SORBITAN SESQUIOLEATE; SORBITAN MONOSTEARATE; SQUALANE; STEARIC ACID; TETRASODIUM GLUTAMATE DIACETATE; TOCOPHEROL; WATER; XANTHAN GUM

SaltyFace Daily Sun Shield Mineral Sunscreen For Face SPF 30

Active Ingredient

Zinc Oxide 14%

Purpose

Sunscreen

Uses

- Helps prevent sunburn.
- Higher SPF gives more sunburn protection
- Retains SPF after 80 minutes of swimming or sweating
- If used as directed with other sun protection measures (see Directions), decreases the risk of skin cancer and early skin aging caused by the sun

Warnings

For external use only

Do not use

- On damaged or broken skin.

When using this product

- keep out of eyes. Rinse with water to remove.
- Do not puncture or incinerate. Contents under pressure. Do not store it at temperatures above 120°F.

Stop use and ask a doctor if

- rash or irritation develops and lasts.

Keep out of reach of children.

- If swallowed, get medical help or contact a Poison Control Center right away.

If pregnant or breast-feeding,

- ask a health professional before use.

Directions

- Apply liberally 15 minutes before sun exposure and as needed.
- Children under 6 months of age: ask a doctor.
- Reapply:
- after 80 minutes of swimming or sweating
- immediately after towel drying
- at least every 2 hours
- Sun Protection Measures.Spending time in the sun increases your risk of skin cancer and early skin aging. To decrease the risk, regularly use a sunscreen with broad spectrum SPF of 15 or higher and other sun protection measures including:
- Limit time in the sun, especially from 10 a.m. - 2 p.m.
- Wear long-sleeved shirts, pants, hats, and sunglasses.

Other Information

- Protect the product in this container from excessive heat and direct sun

Inactive Ingredients

Aloe Barbadensis Leaf Juice, Benzyl Alcohol, Butyloctyl Salicylate, Camellia Sinensis Leaf Extract, Caprylic/Capric Triglyceride, Capryloyl Glycerin/Sebacic Acid Copolymer, Chamomilla Recutita (Matricaria) Flower Extract, Citric Acid, Coco-Caprylate/Caprate, Decyl Glucoside, Dehydroacetic Acid, Dimethicone, Dodecane, Glycerin, Glyceryl Stearate SE, Hydrogenated Lecithin, Isopropyl Myristate, Mangifera Indica (Mango) Seed Butter, Polyacrylate Crosspolymer-6, Polyhydroxystearic Acid, Propanediol, Sodium Hyaluronate, Sodium Stearoyl Glutamate, Sorbitan Sesquioleate, Sorbitan Stearate, Squalane, Stearic Acid, Tetrasodium Glutamate Diacetate, Tocopherol, Water (Aqua), Xanthan Gum.

Questions?

1-778-872-5782